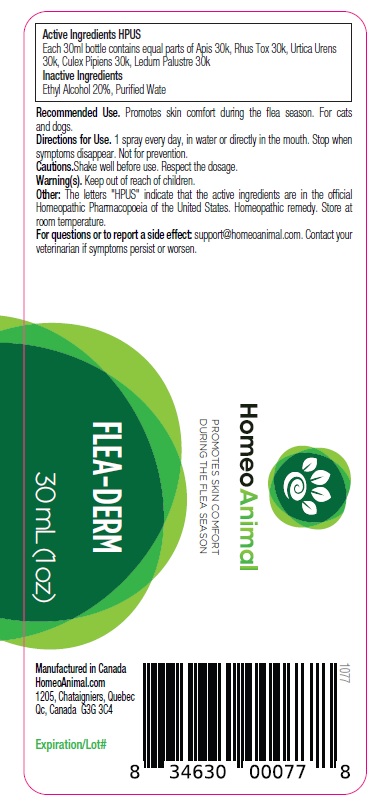 DRUG LABEL: FLEA-DERM
NDC: 86147-031 | Form: LIQUID
Manufacturer: Groupe Cyrenne Inc.
Category: homeopathic | Type: OTC ANIMAL DRUG LABEL
Date: 20230419

ACTIVE INGREDIENTS: APIS MELLIFERA 30 [kp_C]/30 mL; TOXICODENDRON PUBESCENS LEAF 30 [kp_C]/30 mL; URTICA URENS WHOLE 30 [kp_C]/30 mL; CULEX PIPIENS 30 [kp_C]/30 mL; RHODODENDRON TOMENTOSUM LEAFY TWIG 30 [kp_C]/30 mL
INACTIVE INGREDIENTS: ALCOHOL; WATER

Active ingredients

apis 30k, rhus tox 30k, urtica urens 30k, culex pipiens 30k, ledum palustre 30k

Uses

Promotes skin comfort during the flea season. For cats and dogs.

Warnings

Shake well before use. Respect the dosage. Keep out of reach of children.

Direction

1 spray every day, in water or directly in the mouth. Stop when symptoms disappear. Not for prevention.

Inactive ingredients

Ethyl alcohol 20%, purified water

Other information

The letters "HPUS" indicate that the active ingredients are in the official Homeopathic Pharmacopoeia of the United States. Homeopathic remedy. Store at room temperature.